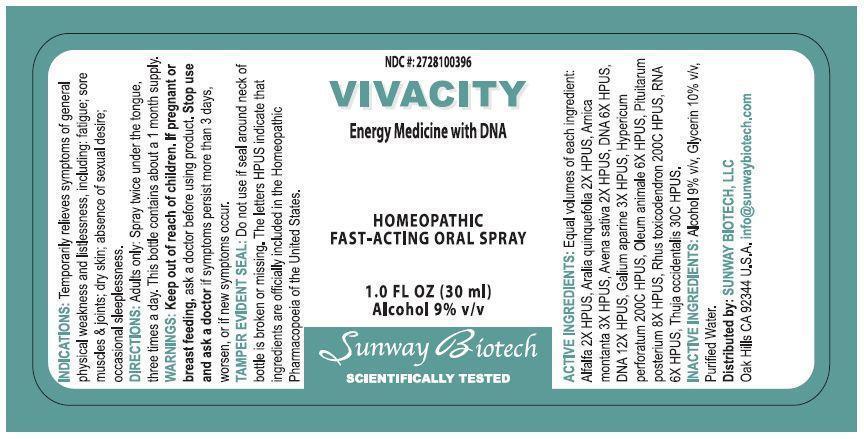 DRUG LABEL: Brain Power
NDC: 55138-001 | Form: SPRAY
Manufacturer: Integra Health International, S.A. de C.V.
Category: homeopathic | Type: HUMAN OTC DRUG LABEL
Date: 20150515

ACTIVE INGREDIENTS: SEMECARPUS ANACARDIUM JUICE 30 [hp_C]/30 mL; ARNICA MONTANA 1.5 [hp_C]/30 mL; CALCIUM FLUORIDE 30 [hp_C]/30 mL; SILYBUM MARIANUM SEED OIL 1.5 [hp_C]/30 mL; CINCHONA OFFICINALIS BARK 3 [hp_C]/30 mL; HERRING SPERM DNA 3 [hp_C]/30 mL; GINKGO 3 [hp_C]/30 mL; EGG PHOSPHOLIPIDS 6 [hp_C]/30 mL; ACHILLEA MILLEFOLIUM 1.5 [hp_C]/30 mL; PHOSPHORIC ACID 30 [hp_C]/30 mL; SACCHAROMYCES CEREVISIAE RNA 6 [hp_C]/30 mL; SILICON DIOXIDE 6 [hp_C]/30 mL; ZINC SULFATE HEPTAHYDRATE 6 [hp_C]/30 mL
INACTIVE INGREDIENTS: ALCOHOL; GLYCERIN; WATER

INDICATIONS AND USAGE

Indications: Temporarily relieves symptoms of general physical weakness and listlessness, including: fatigue; sore muscles & joints; dry skin; absence of sexual desire; occasional sleeplessness.

PURPOSE

NDC#: 2728100396

VIVACITY

Energy Medicine with DNA

Homeopathic Fast-Acting Oral Spray

1.0 Fl Oz (30 mL)

Alcohol 9% v/v

Keep out of reach of children.

DOSAGE AND ADMINISTRATION

Directions: Adults only: spray twice under the tongue, three times a day. This bottle contains about a 1 month supply.

WARNINGS

Warnings: Keep out of reach of children. If pregnant or breast feeding, ask a doctor before using product. Stop use and ask a doctor if symptoms persist more than 3 days, worsen, or if new symptoms occur.

OTHER SAFETY INFORMATION

Tamper Evident Seal: Do not use if seal around neck of bottle is broken or missing. The letters HPUS indicate that ingredients are officially included in the Homeopathic Pharmacopoeia of the United States.

Distributed by SUNWAY BIOTECH, LLC

Oak HIlls CA 92344 U.S.A. info@sunwaybiotech.com

ACTIVE INGREDIENT

Active Ingredients: Equal volumes of each ingredient: Alfalfa 2X HPUS, Aralia Quinquefolia 2X HPUS, Arnica Montana 3X HPUS, Avena Sativa 2X HPUS, DNA 6X HPUS, DNA 12X HPUS, Galium Aparine 3X HPUS, Hypericum Perforatum 200C HPUS, Oleum Animale 6X HPUS, Pituitarium Posterium 8X HPUS, Rhus Toxicodendron 200C HPUS, RNA 6X HPUS, Thuja Occidentalis 30C HPUS.

INACTIVE INGREDIENT

Inactive Ingredients: Alcohol 9% v/v, Glycerin 10% v/v, Purified Water.